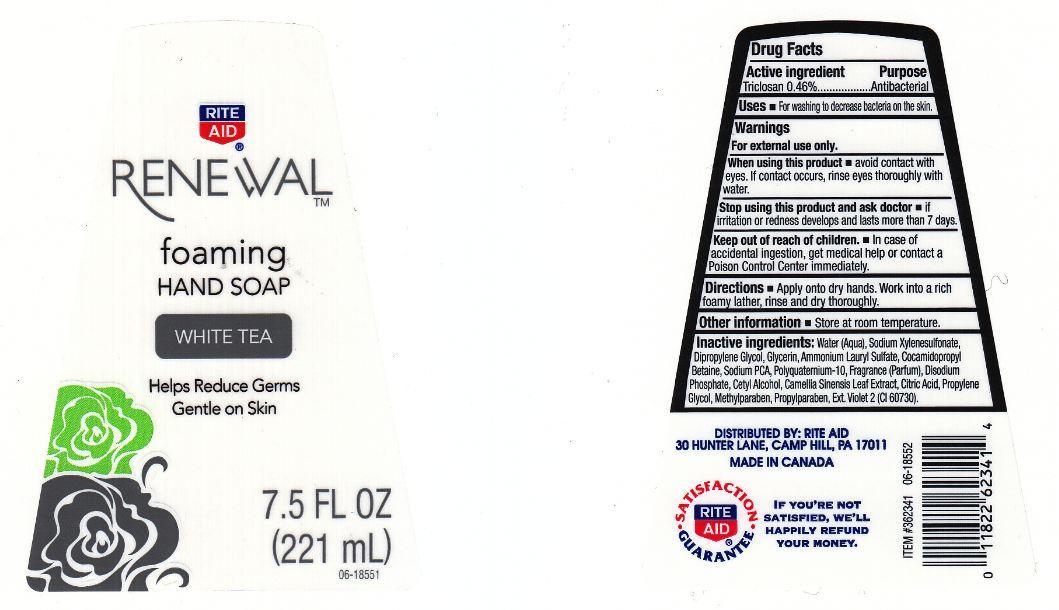 DRUG LABEL: RITE AID RENEWAL
NDC: 11822-1880 | Form: LIQUID
Manufacturer: RITE AID CORPORATION
Category: otc | Type: HUMAN OTC DRUG LABEL
Date: 20130411

ACTIVE INGREDIENTS: TRICLOSAN 4.6 mg/1 mL
INACTIVE INGREDIENTS: WATER; SODIUM XYLENESULFONATE; DIPROPYLENE GLYCOL; GLYCERIN; AMMONIUM LAURYL SULFATE; COCAMIDOPROPYL BETAINE; SODIUM PYRROLIDONE CARBOXYLATE; POLYQUATERNIUM-10 (400 CPS AT 2%); SODIUM PHOSPHATE, DIBASIC, ANHYDROUS; CETYL ALCOHOL; GREEN TEA LEAF; CITRIC ACID MONOHYDRATE; PROPYLENE GLYCOL; METHYLPARABEN; PROPYLPARABEN; D&C VIOLET NO. 2

DRUG FACTS

ACTIVE INGREDIENT

TRICLOSAN 0.46%

PURPOSE

ANTIBACTERIAL

USES

FOR WASHING TO DECREASE BACTERIA ON THE SKIN.

WARNINGS

FOR EXTERNAL USE ONLY.

WHEN USING THIS PRODUCT

AVOID CONTACT WITH EYES. IF CONTACT OCCURS, RINSE EYES THOROUGHLY WITH WATER.

STOP USING THIS PRODUCT AND ASK DOCTOR

IF IRRITATION OR REDNESS DEVELOPS AND LASTS MORE THAN 7 DAYS.

KEEP OUT OF REACH OF CHILDREN

IN CASE OF ACCIDENTAL INGESTION, GET MEDICAL HELP OR CONTACT A POISON CONTROL CENTER IMMEDIATELY.

DIRECTIONS

APPLY ONTO DRY HANDS. WORK INTO A RICH FOAMY LATHER, RINSE AND DRY THOROUGHLY.

OTHER INFORMATION

STORE AT ROOM TEMPERATURE.

INACTIVE INGREDIENTS:

WATER (AQUA), SODIUM XYLENESULFONATE, DIPROPYLENE GLYCOL, GLYCERIN, AMMONIUM LAURYL SULFATE, COCAMIDOPROPYL BETAINE, SODIUM PCA, POLYQUATERNIUM-10, FRAGRANCE (PARFUM), DISODIUM PHOSPHATE, CETYL ALCOHOL, CAMELLIA SINENSIS LEAF EXTRACT, CITRIC ACID, PROPYLENE GLYCOL, METHYLPARABEN, PROPYLPARABEN, EXT. VIOLET 2 (CI 60730).